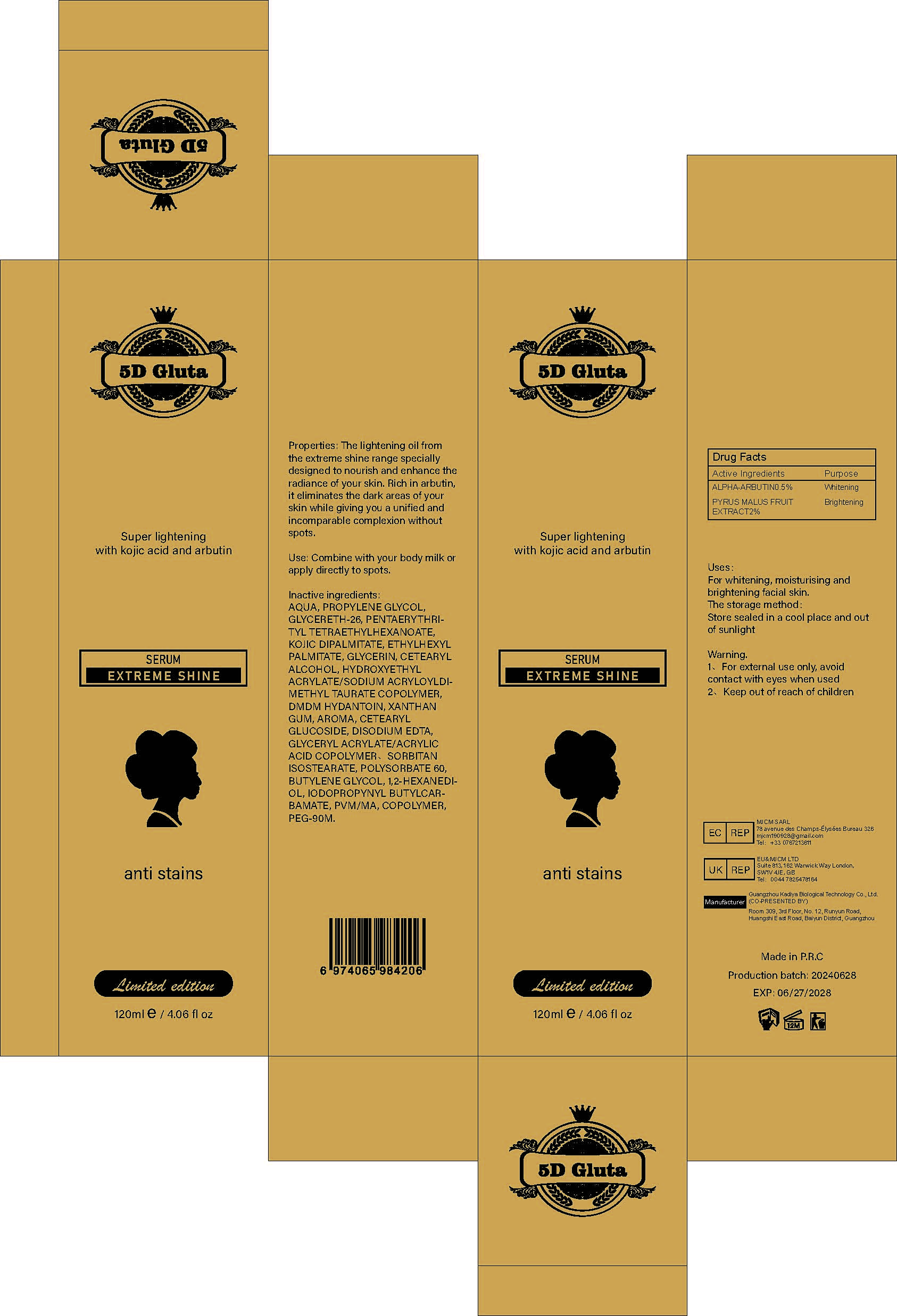 DRUG LABEL: Super lightening with kojic acid and arbutin Serum
NDC: 84423-016 | Form: LIQUID
Manufacturer: Guangzhou Kadiya Biotechnology Co., Ltd.
Category: otc | Type: HUMAN OTC DRUG LABEL
Date: 20240709

ACTIVE INGREDIENTS: ALPHA-ARBUTIN 0.6 mg/120 mg
INACTIVE INGREDIENTS: XANTHAN GUM; IODOPROPYNYL BUTYLCARBAMATE; GLYCERYL ACRYLATE/ACRYLIC ACID COPOLYMER (300000 CP AT 2%); HYDROXYETHYL ACRYLATE/SODIUM ACRYLOYLDIMETHYL TAURATE COPOLYMER (45000 MPA.S AT 1%); DMDM HYDANTOIN; CETEARYL GLUCOSIDE; EDETATE DISODIUM; POLYSORBATE 60; BUTYLENE GLYCOL; POLYETHYLENE GLYCOL 4000000; SORBITAN ISOSTEARATE; 1,2-HEXANEDIOL; WATER; ETHYLHEXYL PALMITATE; GLYCERIN; METHYL VINYL ETHER AND MALEIC ANHYDRIDE COPOLYMER (1100000 WAMW); PENTAERYTHRITYL TETRAETHYLHEXANOATE; CETOSTEARYL ALCOHOL; PROPYLENE GLYCOL

Uses：
For whitening, moisturising and brightening facial skin.

INACTIVE INGREDIENT

AQUA、PROPYLENE GLYCOL、GLYCERETH-26、PENTAERYTHRITYL TETRAETHYLHEXANOATE、KOJIC DIPALMITATE、ETHYLHEXYL PALMITATE、GLYCERIN、CETEARYL ALCOHOL、HYDROXYETHYL ACRYLATE/SODIUM ACRYLOYLDIMETHYL TAURATE COPOLYMER、DMDM HYDANTOIN、XANTHAN GUM、AROMA、CETEARYL GLUCOSIDE、DISODIUM EDTA、GLYCERYL ACRYLATE/ACRYLIC ACID COPOLYMER、SORBITAN ISOSTEARATE、POLYSORBATE 60、BUTYLENE GLYCOL、1,2-HEXANEDIOL、IODOPROPYNYL BUTYLCARBAMATE、PVM/MA、COPOLYMER、PEG-90M

Warning.
1、For external use only, avoid contact with eyes when used
2、Keep out of reach of children

INDICATIONS AND USAGE

Combine with your body milk or apply directly to spots.

KEEP OUT OF REACH OF CHILDREN SECTION

Active Ingredients
ALPHA-ARBUTIN0.5%
PYRUS MALUS FRUIT EXTRACT2%

DOSAGE AND ADMINISTRATION

Combine with vour body milk or apply directly to spots.

Drug Facts
Active Ingredients
ALPHA-ARBUTIN0.5%
PYRUS MALUS FRUIT EXTRACT2%

Uses：
For whitening, moisturising and brightening facial skin.
The storage method：
Store sealed in a cool place and out of sunlight

Warning.
1、For external use only, avoid contact with eyes when used
2、Keep out of reach of children

Inactive ingredients：
AQUA、PROPYLENE GLYCOL、GLYCERETH-26、PENTAERYTHRITYL TETRAETHYLHEXANOATE、KOJIC DIPALMITATE、ETHYLHEXYL PALMITATE、GLYCERIN、CETEARYL ALCOHOL、HYDROXYETHYL ACRYLATE/SODIUM ACRYLOYLDIMETHYL TAURATE COPOLYMER、DMDM HYDANTOIN、XANTHAN GUM、AROMA、CETEARYL GLUCOSIDE、DISODIUM EDTA、GLYCERYL ACRYLATE/ACRYLIC ACID COPOLYMER、SORBITAN ISOSTEARATE、POLYSORBATE 60、BUTYLENE GLYCOL、1,2-HEXANEDIOL、IODOPROPYNYL BUTYLCARBAMATE、PVM/MA、COPOLYMER、PEG-90M